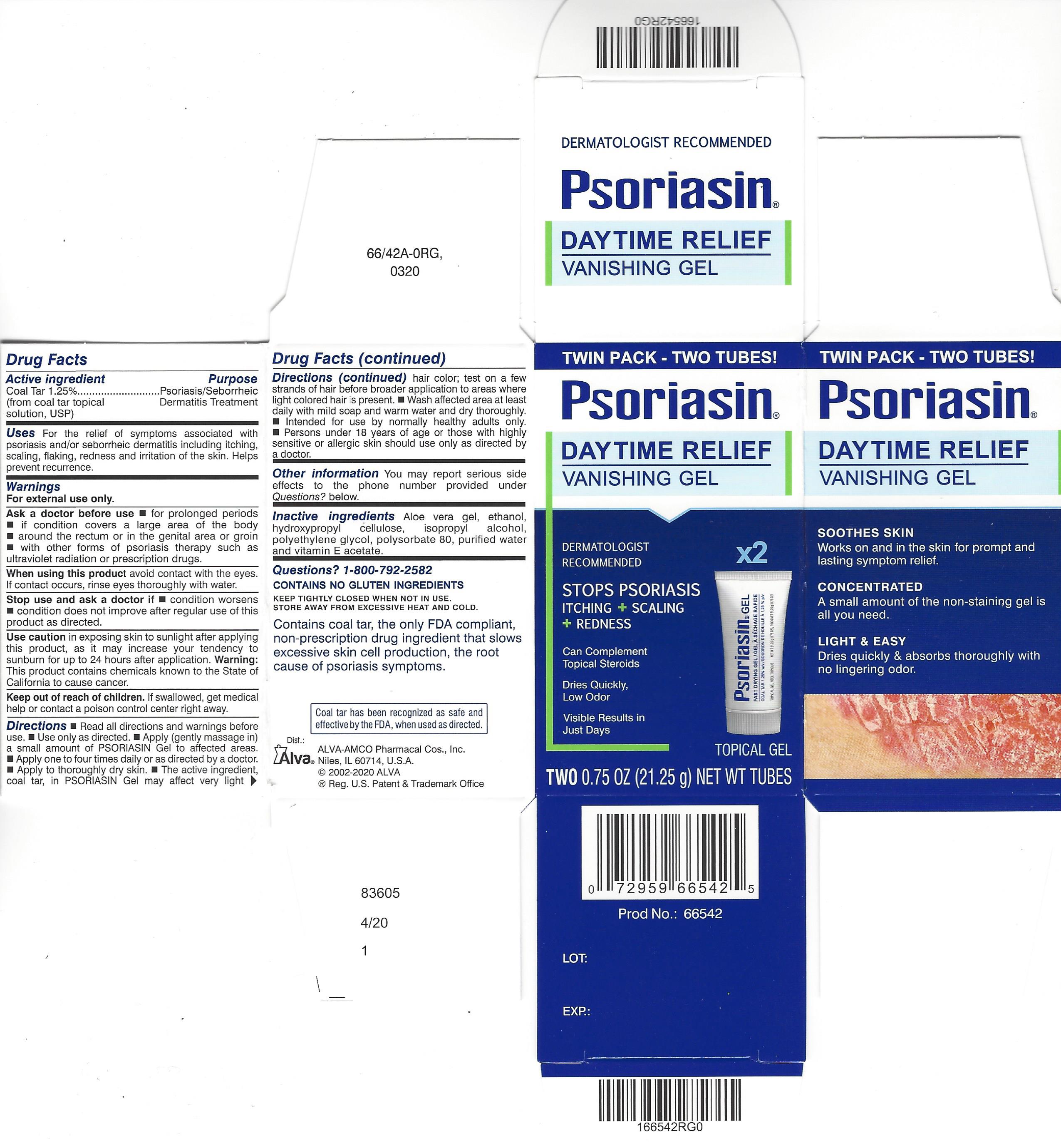 DRUG LABEL: Psoriasin Gel
NDC: 52389-166 | Form: GEL
Manufacturer: Kobayashi Healthcare International, Inc.
Category: otc | Type: HUMAN OTC DRUG LABEL
Date: 20241105

ACTIVE INGREDIENTS: COAL TAR 12.5 mg/1 g
INACTIVE INGREDIENTS: ALOE VERA LEAF; ALCOHOL; HYDROXYPROPYL CELLULOSE (TYPE M); ISOPROPYL ALCOHOL; POLYETHYLENE GLYCOL 400; POLYSORBATE 80; WATER; ALPHA-TOCOPHEROL ACETATE

Psoriasin Gel

Active ingredient

Coal Tar 1.25% (from coal tar topical solution, USP)

Purpose

Psoriasis/Seborrheic Dermatitis Treatment

Uses

For the relief of symptoms associated with psoriasis and/or seborrheic dermatitis including itching, scaling, flaking, redness and irritation of the skin. Helps prevent recurrence.

Warnings

For external use only.

Ask a doctor before use

- for prolonged periods
- if condition covers a large area of the body
- around the rectum or in the genital area or groin
- with other forms of psoriasis therapy such as ultraviolet radiation or prescription drugs.

When using this product avoid contact with the eyes. If contact occurs, rinse eyes thoroughly with water.

Stop use and ask a doctor if

- condition worsens
- condition does not improve after regular use of this product as directed.

Use caution in exposing skin to sunlight after applying this product, as it may increase your tendency to sunburn for up to 24 hours after application.

Warning: This product contains chemicals known to the State of California to cause cancer.

Keep out of reach of children. If swallowed, get medical help or contact a poison control center right away.

Directions

- Read all package directions and warnings before use.
- Use only as directed.
- Apply (gently massage in) a small amount of Psoriasin Gel to affected areas.
- Apply one to four times daily or as directed by a doctor.
- Apply to thoroughly dry skin.
- The active ingredient, coal tar, in Psoriasin Gel may affect very light hair color; test first on a few strands of hair before broader application to areas where light colored hair is present.
- Wash affected area at least daily with mild soap and warm water and dry thoroughly.
- Intended for use by normally healthy adults only.
- Persons under 18 years of age or those with highly sensitive or allergic skin should use only as directed by a doctor.

Other Information

You may report serious side effects to the phone number provided under Questions? below.

Inactive ingredients

Aloe vera gel, ethanol, hydroxypropyl cellulose, isopropyl alcohol, polyethylene glycol, polysorbate 80, purified water and vitamin E acetate.

Questions?

1-800-792-2582

Package Insert

Psoriasin

DAYTIME RELIEF VANISHING GEL

DERMATOLOGIST RECOMMENDED

- Stops Psoriasis itching, scaling, redness
- Can complement topical steroids
- Dries quickly, low odor
- Visible results in just days
- Helps prevent recurrence

Psoriasin Daytime Relief Vanishing Gel gets to work quickly to help stop the itching, flaking, redness and related discomforts associated with psoriasis. Formulated in a vanishing gel base with aloe and vitamin E, it applies easily, dries quickly and absorbs thoroughly, leaving no greasy appearance or lingering odor. Use Psoriasin Daytime Relief Vanishing Gel with confidence to relieve symptoms of psoriasis and help restore you skin to a more natural looking appearance.

How Coal Tar Works

The coal tar in Psoriasin Daytime Relief Vanishing Gel slows down the excessive skin cell production that is the root cause of psoriasis symptoms. No other FDA compliant non-prescription drug ingredient works this way. Slowing excesive skin cell production means it can help reduce the itching, scaling and redness of psoriasis. With regular use as directed, Psoriasin Daytime Relief Vanishing Gel can even help prevent recurrence of psoriasis symptoms. And coal tar can be used to complement topical steroid therapies.

The Role of Topical Steroids

Topical steroids - similar to the natural corticosteroid hormones produced by the adrenal glands - are a frequently used psoriasis symptom treatment. Topical steroids are used as anti-inflammatory agents to reduce the swelling and redness of lesions. Although topical steroids can produce rapid symptom relief, continuous use of them may cause potential side effects such as skin thinning.

Topical Therapy Choices for Psoriasis Symptom Control

Due to the well documented side effects of topical steroids, some experts recommend using intermittent therapy (also called weekend or pulse therapy). This type of treatment involves applying a topical steroid for three consecutive days each week followed by four days of a coal tar medication like Psoriasin Daytime Relief Vanishing Gel. Ask your doctor if this approach might be right for you.

PSORIASIS SELF-CARE TIPS

In addition to psoriasis treatments recommended by a doctor, you can help reduce psoriasis symptoms by using self-care approaches, including:

Keep Skin Moisturized

Using a moisturizer is an important part of self-care for psoriasis. Dry skin makes irritation and itching caused by psoriasis worse than it needs to be. A vicious cycle can result: dry skin can cause itching and scratching, leading to new psoriasis patches developing on the irritated skin. Dermatologists recommend ointments and heavy creams to lock water into the skin.

Bathe with Care

Too many baths and showers can dry your skin. Here are a few suggestions:

- Don't bathe or shower with hot water, which can irritate. Use lukewarm water instead.
- Don't dry off by rubbing with a towel. Pat yourself somewhat dry and then apply cream.
- Plain water can dry your skin. Adding salts, oil, or finely ground oatmeal to bath water can help to soothe your skin.
- Take fewer showers and baths. They can strip your skin of natural oils. Bathe every other day or every third day, especially during the winter months.

Reduce Stress

Stress can cause psoriasis to flare for the first time or aggravate existing psoriasis. Relaxation and stress reduction may help prevent stress from making your psoriasis symptoms worse.

- Engage in relaxation techniques, such as yoga, meditation, or massage
- Excercise regularly
- Get enough sleep

Be Smart About Sunlight

The ultraviolet rays in sunlight slow the growth of skin cells, so getting moderate doses of sun is good. But make it brief and use sunscreen, because sunburn can trigger psoriasis flare-ups. Some medications can make your skin more sensitive to ultraviolet rays, so talk to your doctor first.

Stick to the Plan

Applying creams and ointments day after day can be inconvenient. But compliance is the key for topical therapies. Once you have a topical treatment regimen that's working for you, making it part of you daily routine can improve results. Also, topical therapies help you avoid the potential side effects of systemic treatments for psoriasis.

The active ingredient in Psoriasin Daytime Relief Vanishing Gel has been recognized to be safe and effective by an FDA Expert Advisory Panel when used as directed.

USE THE FAMILY OF PSORIASIN PRODUCTS TO BUILD YOUR PSORIASIS TREATMENT REGIMEN:

- PSORIASIN PROBLEM SKIN FORMULA CREAM Combines a low dose of coal tar with botanicals & Vitamin D3 in a soothing cream that won't irritate sensitive skin
- PSORIASIN DEEP MOISTURIZING OINTMENT Delivers coal tar in a base that locks in moisture for hours to help restore your skin's appearance
- PSORIASIN DAYTIME RELIEF VANISHING GEL Is a quick-drying, low-odor coal tar therapy

WWW.PSORIASIN.COM